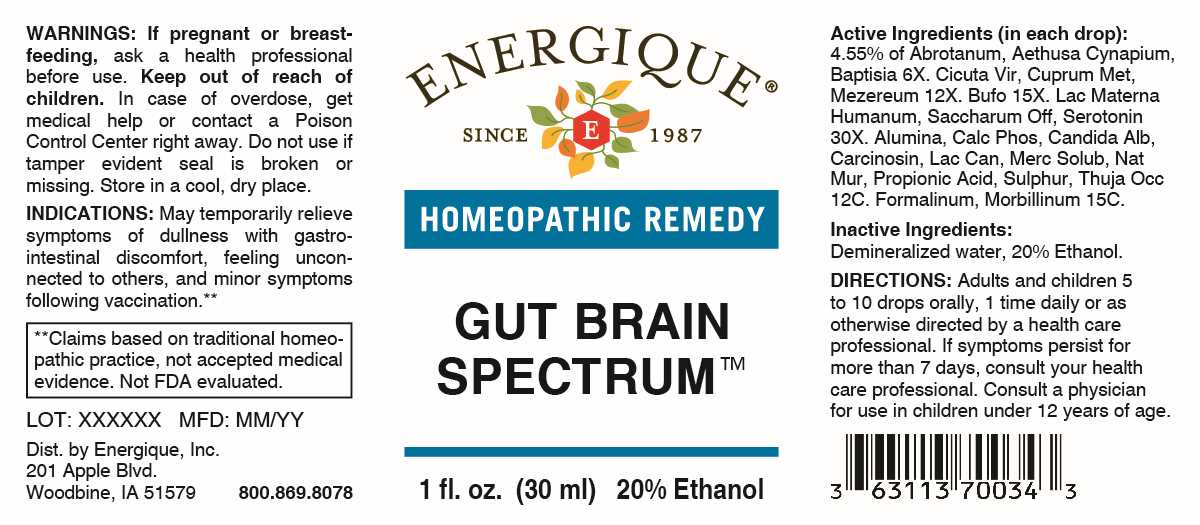 DRUG LABEL: Gut Brain Spectrum
NDC: 44911-0726 | Form: LIQUID
Manufacturer: Energique, Inc.
Category: homeopathic | Type: HUMAN OTC DRUG LABEL
Date: 20241226

ACTIVE INGREDIENTS: ARTEMISIA ABROTANUM FLOWERING TOP 6 [hp_X]/1 mL; AETHUSA CYNAPIUM WHOLE 6 [hp_X]/1 mL; BAPTISIA TINCTORIA ROOT 6 [hp_X]/1 mL; CICUTA VIROSA ROOT 12 [hp_X]/1 mL; COPPER 12 [hp_X]/1 mL; DAPHNE MEZEREUM BARK 12 [hp_X]/1 mL; BUFO BUFO CUTANEOUS GLAND 15 [hp_X]/1 mL; HUMAN MILK 30 [hp_X]/1 mL; SUCROSE 30 [hp_X]/1 mL; SEROTONIN HYDROCHLORIDE 30 [hp_X]/1 mL; ALUMINUM OXIDE 12 [hp_C]/1 mL; TRIBASIC CALCIUM PHOSPHATE 12 [hp_C]/1 mL; CANDIDA ALBICANS 12 [hp_C]/1 mL; HUMAN BREAST TUMOR CELL 12 [hp_C]/1 mL; CANIS LUPUS FAMILIARIS MILK 12 [hp_C]/1 mL; MERCURIUS SOLUBILIS 12 [hp_C]/1 mL; SODIUM CHLORIDE 12 [hp_C]/1 mL; PROPIONIC ACID 12 [hp_C]/1 mL; SULFUR 12 [hp_C]/1 mL; THUJA OCCIDENTALIS LEAFY TWIG 12 [hp_C]/1 mL; FORMALDEHYDE SOLUTION 15 [hp_C]/1 mL; MEASLES VIRUS 15 [hp_C]/1 mL
INACTIVE INGREDIENTS: WATER; ALCOHOL

DRUG FACTS:

ACTIVE INGREDIENTS:

(in each drop): 4.55% of Abrotanum 6X, Aethusa Cynapium 6X, Baptisia Tinctoria 6X. Cicuta Virosa 12X, Cuprum Metallicum 12X, Mezereum 12X. Bufo Rana 15X. Lac Materna Humanum 30X, Saccharum Officinale 30X, Serotonin 30X. Alumina 12C, Calcarea Phosphorica 12C, Candida Albicans 12C, Carcinosin 12C, Lac Caninum 12C, Mercurius Solubilis 12C, Natrum Muriaticum 12C, Propionic Acid 12C, Sulphur 12C, Thuja Occidentalis 12C. Formalinum 15C, Morbillinum 15C.

PURPOSE:

May temporarily relieve symptoms of dullness with gastro-intestinal discomfort, feeling unconnected to others, and minor symptoms following vaccination.**

**Claims based on traditional homeopathic practice, not accepted medical evidence. Not FDA evaluated.

WARNINGS:

If pregnant or breast-feeding, ask a health professional before use.

Keep out of reach of children. In case of overdose, get medical help or contact a Poison Control Center right away.

Do not use if tamper evident seal is broken or missing.

Store in a cool, dry place.

KEEP OUT OF REACH OF CHILDREN:

In case of overdose, get medical help or contact a Poison Control Center right away.

DIRECTIONS:

Adults and children 5 to 10 drops orally, 1 time daily or as otherwise directed by a health care professional. If symptoms persist for more than 7 days, consult your health care professional. Consult a physician for use in children under 12 years of age.

INDICATIONS:

May temporarily relieve symptoms of dullness with gastro-intestinal discomfort, feeling unconnected to others, and minor symptoms following vaccination.**

**Claims based on traditional homeopathic practice, not accepted medical evidence. Not FDA evaluated.

INACTIVE INGREDIENTS:

Demineralized water, 20% Ethanol

QUESTIONS:

Dist. by Energique, Inc.

201 Apple Blvd.

Woodbine, IA 51579

800.869.8078

PACKAGE DISPLAY LABEL:

ENERGIQUE

SINCE 1987

HOMEOPATHIC REMEDY

GUT BRAIN

SPECTRUM

1 fl. oz. (30 ml)